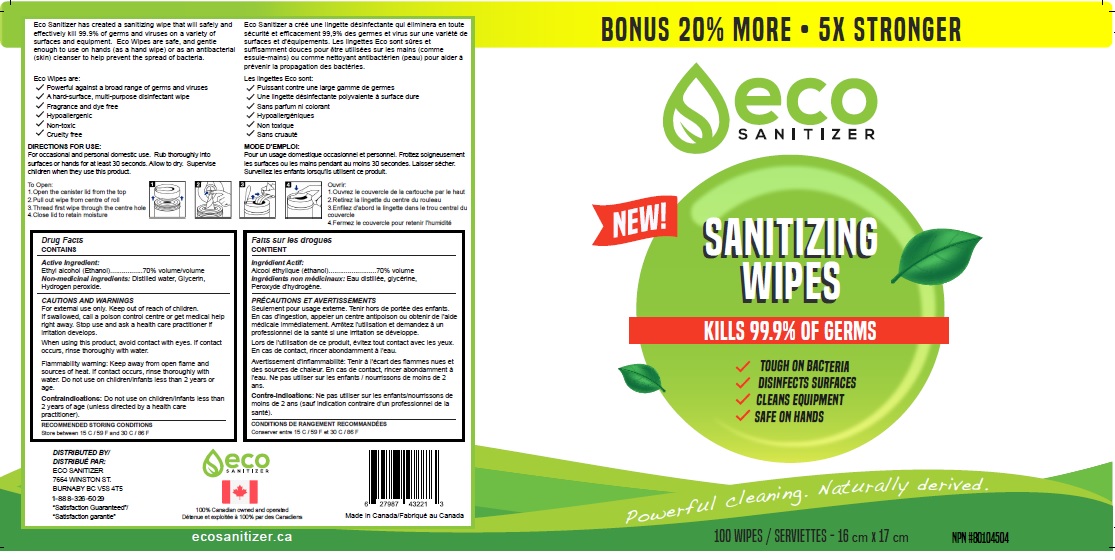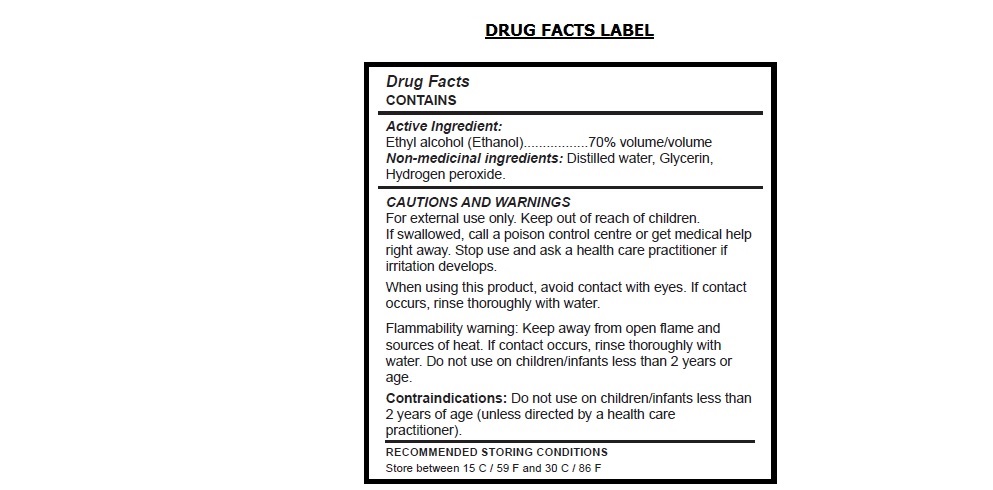 DRUG LABEL: Eco Sanitizer Sanitizing Wipes
NDC: 80731-003 | Form: CLOTH
Manufacturer: 0966452 B.C. Ltd.
Category: otc | Type: HUMAN OTC DRUG LABEL
Date: 20201019

ACTIVE INGREDIENTS: ALCOHOL 70 mL/100 mL
INACTIVE INGREDIENTS: WATER; GLYCERIN; HYDROGEN PEROXIDE

eco SANITIZER SANITIZING WIPES

Active Ingredient:

Ethyl alcohol (Ethanol) 70% volume/volume

INACTIVE INGREDIENT

Non-medicinal ingredients: Distilled water, Glycerin, Hydrogen peroxide.

Purpose: Antibacterial

INDICATIONS AND USAGE

Use: Cleanser to help prevent the spread of bacteria

CAUTIONS AND WARNINGS

For external use only.

Stop use and ask a health care practitioner if irritation develops.

When using this product, avoid contact with eyes. If contact occurs, rinse thoroughly with water.

Flammability warning: Keep away from open flame and sources of heat. If contact occurs, rinse thoroughly with water. Do not use on children/infants less than 2 years or age.

Contraindications: Do not use on children/infants less than 2 years of age (unless directed by a health care practitioner).

Keep out of reach of children. If swallowed, call a poison control centre or get medical help right away.

DOSAGE AND ADMINISTRATION

DIRECTIONS FOR USE:

For occasional and personal domestic use. Rub thoroughly into surfaces or hands for at least 30 seconds. Allow to dry. Supervise children when they use this product.

RECOMMENDED STORING CONDITIONS

Store between 15 C / 59 F and 30 C / 86 F

BONUS 20% MORE • 5X STRONGER

NEW!

KILLS 99.9% OF GERMS

√ TOUGH ON BACTERIA

√ DISINFECTS SURFACES

√ CLEANS EQUIPMENT

√ SAFE ON HANDS

Powerful cleaning. Naturally derived.

Eco Sanitizer has created a sanitizing wipe that will safely and effectively kill 99.9% of germs and viruses on a variety of surfaces and equipment. Eco Wipes are safe, and gentle enough to use on hands (as a hand wipe) or as an antibacterial (skin) cleanser to help prevent the spread of bacteria.

Eco Wipes are:

√ Powerful against a broad range of germs and viruses
√ A hard-surface, multi-purpose disinfectant wipe
√ Fragrance and dye free
√ Hypoallergenic
√ Non-toxic
√ Cruelty free

To Open:
1.Open the canister lid from the top
2.Pull out wipe from centre of roll
3.Thread first wipe through the centre hole
4.Close lid to retain moisture

DISTRIBUTED BY:

ECO SANITIZER

7664 WINSTON ST.

BURNABY BC V5S 4T5

1-888-326-5029

“Satisfaction Guaranteed”

100% Canadian owned and operated

Made in Canada

ecosanitizer.ca